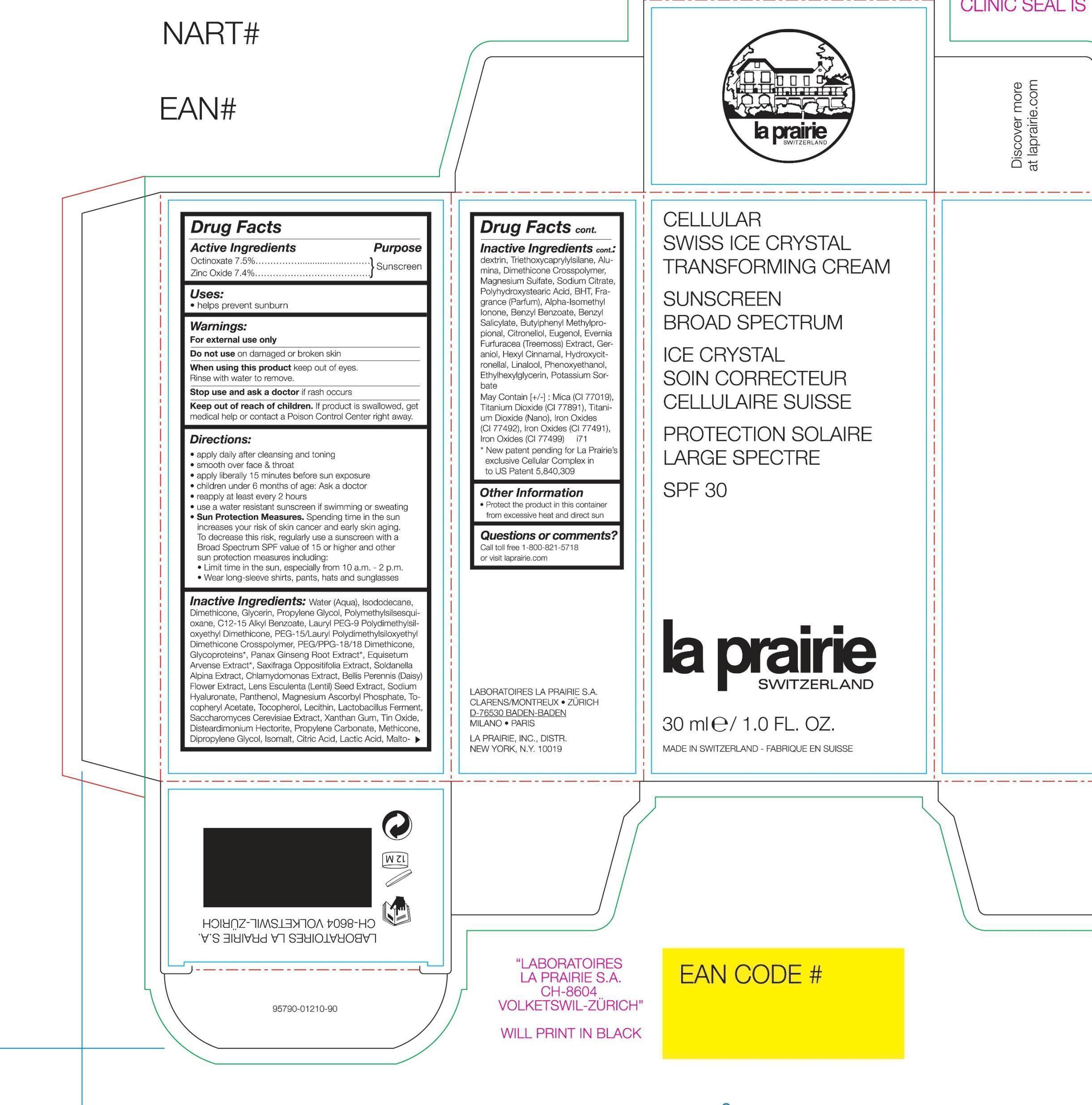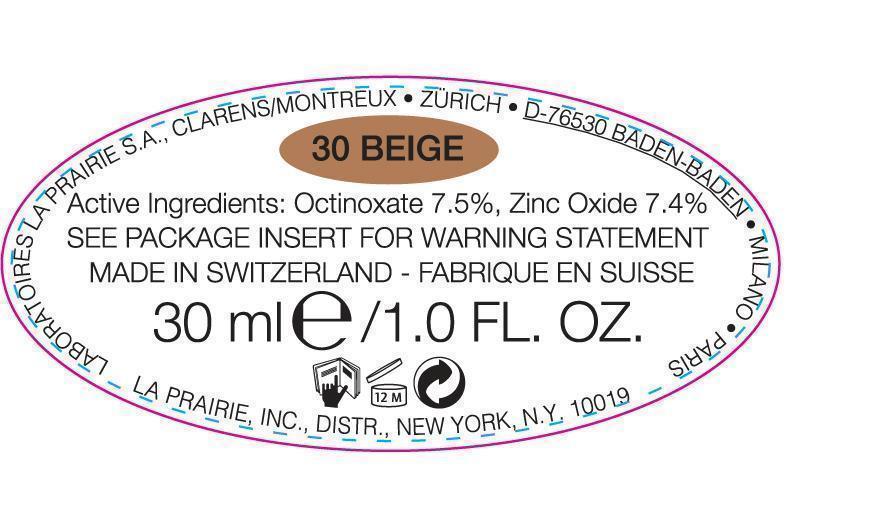 DRUG LABEL: Cellular Swiss Sunscreen
NDC: 68807-311 | Form: CREAM
Manufacturer: Temmentec Ag
Category: otc | Type: HUMAN OTC DRUG LABEL
Date: 20170109

ACTIVE INGREDIENTS: OCTINOXATE 7.5 g/78.4 kg; ZINC OXIDE 7.4 g/78.4 kg
INACTIVE INGREDIENTS: WATER; ISODODECANE; DIMETHICONE; GLYCERIN; PROPYLENE GLYCOL; ALKYL (C12-15) BENZOATE; LAURYL PEG-9 POLYDIMETHYLSILOXYETHYL DIMETHICONE; PEG/PPG-18/18 DIMETHICONE; ASIAN GINSENG; EQUISETUM ARVENSE BRANCH; BELLIS PERENNIS FLOWER; LENTIL; HYALURONATE SODIUM; PANTHENOL; MAGNESIUM ASCORBYL PHOSPHATE; .ALPHA.-TOCOPHEROL ACETATE; TOCOPHEROL; SACCHAROMYCES CEREVISIAE; XANTHAN GUM; STANNIC OXIDE; DISTEARDIMONIUM HECTORITE; PROPYLENE CARBONATE; METHICONE (20 CST); DIPROPYLENE GLYCOL; ISOMALT; CITRIC ACID MONOHYDRATE; LACTIC ACID; MALTODEXTRIN; TRIETHOXYCAPRYLYLSILANE; DIMETHICONE CROSSPOLYMER (450000 MPA.S AT 12% IN CYCLOPENTASILOXANE); MAGNESIUM SULFATE; SODIUM CITRATE; BUTYLATED HYDROXYTOLUENE; ISOMETHYL-.ALPHA.-IONONE; BENZYL BENZOATE; BENZYL SALICYLATE; BUTYLPHENYL METHYLPROPIONAL; .BETA.-CITRONELLOL, (R)-; EUGENOL; PSEUDEVERNIA FURFURACEA; GERANIOL; .ALPHA.-HEXYLCINNAMALDEHYDE; HYDROXYCITRONELLAL; LINALOOL, (+/-)-; PHENOXYETHANOL; ETHYLHEXYLGLYCERIN; POTASSIUM SORBATE; MICA; TITANIUM DIOXIDE; FERRIC OXIDE YELLOW; FERRIC OXIDE RED; FERROSOFERRIC OXIDE

Cellular Swiss Ice Crystal Transforming Cream SPF30 - BEIGE

Active Ingredients Purpose

Octinoxate 7.5% Sunscreen

Zinc Oxide 7.4% Sunsceen

PURPOSE

Helps prevent sunburn

Keep out of reach of children. if product is swallowed, get medical help or contact a Poison Control Center right away.

Stop use and ask a doctor if rash occurs

WARNINGS

- For external use only

- Do not use on damaged or broken skin

- When using this product keep out of eyes. Rinse with water to remove

Directions

apply daily after cleansing and toning

smooth over face & throat

apply liberally 15 minutes before sun exposure

Children under 6 months of age: Ask a doctor

Reapply at least every 2 hoursuse a water resistant sunscreen if swimming or sweating

Sun Protection Measures. Spending time in the sun increases your risk of skin cancer and early skin aging. To decrease this risk, regularly use a sunscreen with a Broad Spectrum SPF value of 15 or higher and other sun protection measures including:

Limit time in the sun, especially from 10 a.m. - 2 p.m.

Weare long-sleeve shirts, pants, hats and sunglasses

INACTIVE INGREDIENT

Water (Aqua), Isododecane, Dimethicone, Glycerin, Propylene Glycol, Polymethylsilsesquioxane, C12-15 Alkyl Benzoate, Lauryl PEG-9 Polydimethylsiloxyethyl Dimethicone, PEG-15/LaurylPolydimethylsiloxyethyl Dimethicone Crosspolymer, PEG/PPG-18/18 Dimethicone, Glycoproteins*, Panax Ginseng Root Extract*, Equisetum Arvense Extract*, Saxifraga Oppositifolia Extract, Soldanella Alpina Extract, Chlamydomonas Extract, Bellis Pereniis (Daisy) Flower Extract, Lens Esculenta (Lentil Seed Extract, Sodium Hyaluronate, Panthenol, Magnesium Ascorbyl Phosphate, Tocopheryl Acetate, Tocopherol, Lecithin, Lactobacillus Ferment, Saccharomyces Cerevisiae Extract, Xanthan Gum, Tin Oxide, Disteardimonium Hectorite, Propylene Carbonate, Methicone, Dipropylene Glycol, Isomalt, Citric Acid, Lactic Acid, Maltodextrin, Triethoxycaprylylsilane, Alumina, Dimethicon Crosspolymer, Magnesium Sulfate, Sodim Citrate, Polyhydroxystearic Acid, BHT, Fragrance (Parfum), Alpha-Isomethyl Ionone, Benzyl Benzoate, Benzyl Salicylate, Butylphenyl Methylpropaional, Citonellol, Eugenol, Evernia Furfuracea (Treemoss) Extract, Geraniol, Hexyl Cinnamal, Hydroxycitronellal, Linalool, Phenoxyethanol, Ethylhexylglycerin, Potassium Sorbate

May Contain:

Mica (CI 77019), Titanium Dioxide (CI 77891), Titanium Dioxide (Nano), Iron Oxides (CI 77492), Iron Oxides (CI 77491), Iron Oxides (CI 77499)

PACKAGE LABEL

Cellular Swiss Ice Crystal Transforming Cream

Sunscreen

Broad Spectrum

SPF 30

50 ml / 1.7 FL OZ